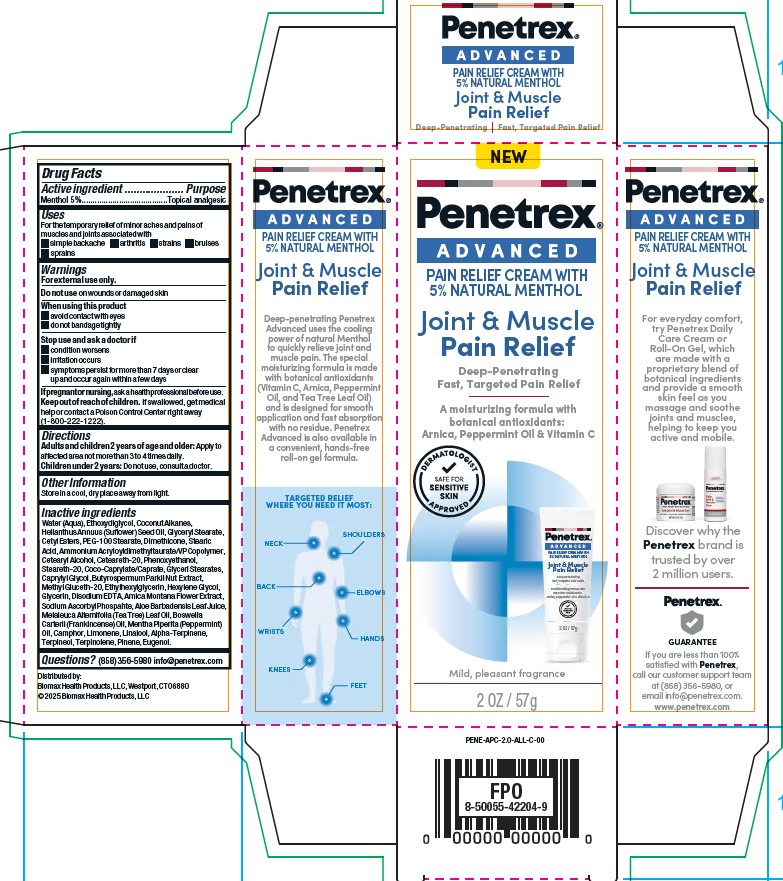 DRUG LABEL: Advanced Pain Relief Cream With 5 % Natural Menthol
NDC: 62742-4278 | Form: CREAM
Manufacturer: Allure Labs
Category: otc | Type: HUMAN OTC DRUG LABEL
Date: 20260225

ACTIVE INGREDIENTS: MENTHOL 5 g/100 g
INACTIVE INGREDIENTS: PEG-100 STEARATE; AMMONIUM ACRYLOYLDIMETHYLTAURATE/VP COPOLYMER; WATER; COCO-CAPRYLATE/CAPRATE; ETHOXYDIGLYCOL; DIMETHICONE; STEARIC ACID; ARNICA MONTANA FLOWER; CAMPHOR (NATURAL); HEXYLENE GLYCOL; MELALEUCA ALTERNIFOLIA (TEA TREE) LEAF OIL; GLYCERIN; CETEARYL ALCOHOL; CETEARETH-20; LINALOOL, (+)-; COCONUT ALKANES; GLYCERYL STEARATE; TERPINOLENE; BUTYROSPERMUM PARKII (SHEA) OIL; BOSWELLIA CARTERII OIL; LIMONENE, (+)-; CETYL ESTERS; ETHYLHEXYLGLYCERIN; ALOE BARBADENSIS LEAF JUICE; TERPINEOL; EDETATE DISODIUM; SODIUM ASCORBYL PHOSPHATE; MENTHA PIPERITA (PEPPERMINT) OIL; METHYL GLUCETH-20; PINENE; ALPHA-TERPINENE; CAPRYLYL GLYCOL; EUGENOL; HELIANTHUS ANNUUS (SUNFLOWER) SEED OIL; PHENOXYETHANOL; STEARETH-20

Drug Facts

Active ingredient;

Menthol - 5%

Purpose:

Topical analgesic

Uses:

For the temporary relief of minor aches and pains of muscles and joints associated with

simple backache

arthritis

strains

bruises

sprains

Warnings:

For external use only

Do not use on wounds or damaged skin

When using this product:

avoid contact with eyes

do not bandage tightl

Stop use and ask a doctor if

condition worsens

irritation occurs

symptoms persist for more than 7 days or clear up and occur again within a few days

Keep out of reach of children. If swallowed, get medical help or contact a Poison Control Center right away

DOSAGE AND ADMINISTRATION

Directions Adults and children 2 years of age and older: Apply to affected area not more than 3 to 4 times daily.

Children under 2 years: Do not use, consult a doctor.

Other Information:

If pregnant or nursing, ask a health professional before use.

Store in a cool, dry place away from light

Inactive ingredients:

Water (Aqua), Ethoxydiglycol, Coconut Alkanes, Helianthus Annuus (Suflower) Seed Oil, Glyceryl Stearate, Cetyl Esters, PEG-100 Stearate, Dimethicone, Stearic Acid, Ammonium Acryloyldimethyltaurate/VP Copolymer, Cetearyl Alcohol, Ceteareth-20, Phenoxyethanol, Steareth-20, Coco-Caprylate/Caprate, Glycerl Stearates, Caprylyl Glycol, Butyrospermum Parkii Nut Extract, Methyl Gluceth-20, Ethylhexylglycerin, Hexylene Glycol, Glycerin, Disodium EDTA, Amica Montana Flower Extract, Sodium Ascorbyl Phospahte, Aloe Barbadensis Leaf Juice, Melaleuca Alternifolia (Tea Tree) Leaf Oil, Boswella Carterii (Frankincense) Oil, Mentha Piperita (Peppermint) Oil, Camphor, Limonene, Linalool, Alpha-Terpinene, Terpineol, Terpinolene, Pinene, Eugenol.